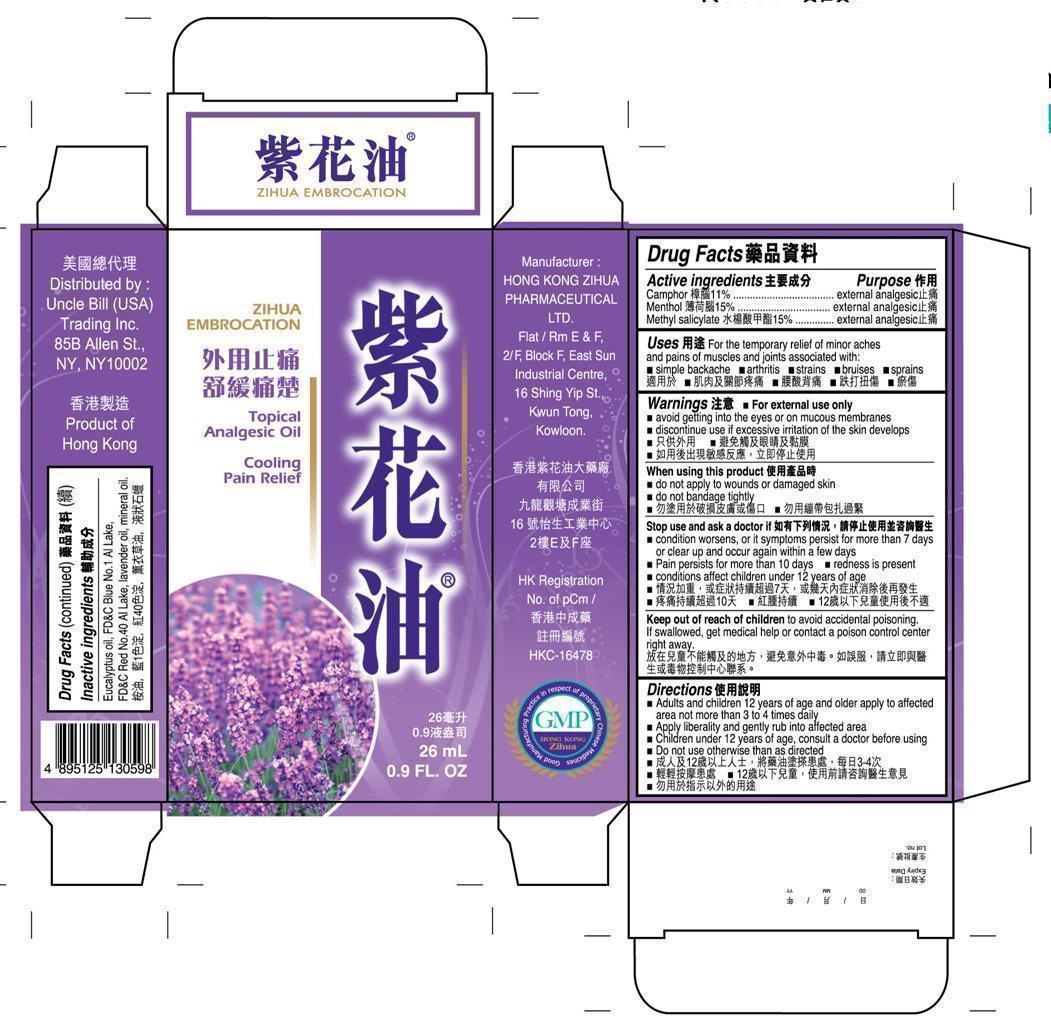 DRUG LABEL: ZIHUA EMBROCATION
NDC: 49980-003 | Form: OIL
Manufacturer: Hong Kong Zihua Pharmaceutical Ltd.
Category: otc | Type: HUMAN OTC DRUG LABEL
Date: 20140421

ACTIVE INGREDIENTS: CAMPHOR (SYNTHETIC) 11 g/100 mL; MENTHOL 15 g/100 mL; METHYL SALICYLATE 15 g/100 mL
INACTIVE INGREDIENTS: EUCALYPTUS OIL; FD&C BLUE NO. 1; FD&C RED NO. 40; LAVENDER OIL; MINERAL OIL

Drug Facts

Active Ingredients

Camphor 11%

Menthol 15%

Methyl salicylate 15%

Purpose

external analgesic

external analgesic

external analgesic

Uses

For the temporary relief of minor aches and pains of muscles and joints associated with:

■ simple backache ■ arthritis ■ strains ■ bruises ■ sprains

Warnings

■ For external use only

■ avoid getting into the eyes or on mucous membranes

■ discontinue use if excessive irritation of the skin develops

When using this product

■ do not apply to wound or damaged skin.

■ do not bandage tightly

Stop use and ask a doctor if

■ condition worsens, or if symptoms persist for more than 7 days or clear up and occur again within a few days

■ Pain persists for more than 10 days conditions

■ redness is present

■ conditions affect children under 12 years of age

Keep out of reach of children

to avoid accidental poisoning. If swallowed, get medical help or contact a poison control center right away.

Directions

■ Adults and children 12 years of age and older apply to affected area not more than 3 to 4 time daily

■ Apply liberally and gently rub into affected area

■ Children under 12 years of age, consult a doctor before using

■ Do not use otherwise than as directed

Inactive ingredients

Eucalyptus oil, FDC Blue No. 1 Al Lake, FDC Red No. 40 Al Lake, lavender oil, mineral oil